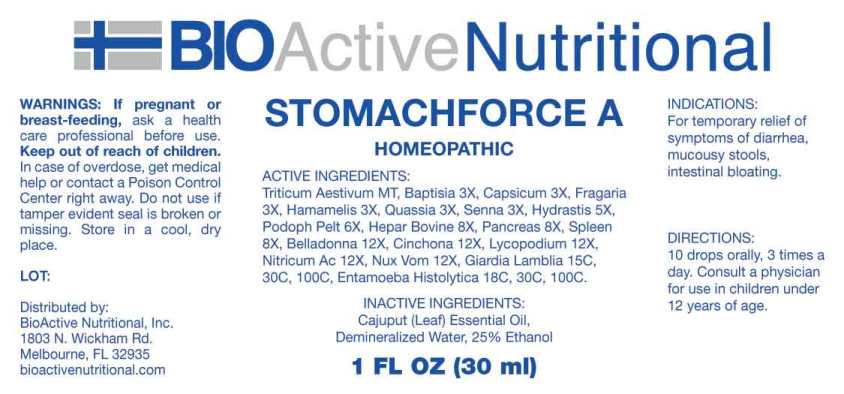 DRUG LABEL: Stomachforce A
NDC: 43857-0601 | Form: LIQUID
Manufacturer: BioActive Nutritional, Inc.
Category: homeopathic | Type: HUMAN OTC DRUG LABEL
Date: 20240419

ACTIVE INGREDIENTS: TRITICUM AESTIVUM WHOLE 1 [hp_X]/1 mL; BAPTISIA TINCTORIA ROOT 3 [hp_X]/1 mL; CAPSICUM 3 [hp_X]/1 mL; FRAGARIA VESCA FRUIT 3 [hp_X]/1 mL; HAMAMELIS VIRGINIANA ROOT BARK/STEM BARK 3 [hp_X]/1 mL; QUASSIA AMARA WOOD 3 [hp_X]/1 mL; SENNA LEAF 3 [hp_X]/1 mL; GOLDENSEAL 5 [hp_X]/1 mL; PODOPHYLLUM 6 [hp_X]/1 mL; BEEF LIVER 8 [hp_X]/1 mL; SUS SCROFA PANCREAS 8 [hp_X]/1 mL; BOS TAURUS SPLEEN 8 [hp_X]/1 mL; ATROPA BELLADONNA 12 [hp_X]/1 mL; CINCHONA OFFICINALIS BARK 12 [hp_X]/1 mL; LYCOPODIUM CLAVATUM SPORE 12 [hp_X]/1 mL; NITRIC ACID 12 [hp_X]/1 mL; STRYCHNOS NUX-VOMICA SEED 12 [hp_X]/1 mL; GIARDIA LAMBLIA 15 [hp_C]/1 mL; ENTAMOEBA HISTOLYTICA 18 [hp_C]/1 mL
INACTIVE INGREDIENTS: MELALEUCA CAJUPUTI LEAF OIL; WATER; ALCOHOL

DRUG FACTS:

ACTIVE INGREDIENTS:

Triticum Aestivum MT, Baptisia Tinctoria 3X, Capsicum Annuum 3X, Fragaria Vesca 3X, Hamamelis Virginiana 3X, Quassia (Amara) 3X, Senna (Cassia Angustifolia) 3X, Hydrastis Canadensis 5X, Podophyllum Peltatum 6X, Hepar Bovine 8X, Pancreas Suis 8X, Spleen (Bovine) 8X, Belladonna 12X, Cinchona Officinalis 12X, Lycopodium Clavatum 12X, Nitricum Acidum 12X, Nux Vomica 12X, Giardia Lamblia 15C, 30C, 100C, Entamoeba Histolytica 18C, 30C, 100C.

INDICATIONS:

For temporary relief of symptoms of diarrhea, mucousy stools, intestinal bloating.

WARNINGS:

If pregnant or breast-feeding, ask a health care professional before use.

Keep out of reach of children. In case of overdose, get medical help or contact a Poison Control Center right away.

Do not use if tamper evident seal is broken or missing.

Store in cool, dry place.

KEEP OUT OF REACH OF CHILDREN:

In case of overdose, get medical help or contact a Poison Control Center right away.

DIRECTIONS:

10 drops orally, 3 times a day. Consult a physician for use in children under 12 years of age.

INDICATIONS:

For temporary relief of symptoms of diarrhea, mucousy stools, intestinal bloating.

INACTIVE INGREDIENTS:

Cajuput (Leaf) Essential Oil, Demineralized Water, 25% Ethanol

QUESTIONS:

Distributed by:

BioActive Nutritional, Inc.

1803 N. Wickham Rd.

Melbourne, FL 32935

bioactivenutritional.com

PACKAGE LABEL DISPLAY:

BIOActive Nutritional

STOMACHFORCE A

HOMEOPATHIC

1 FL OZ (30 ml)